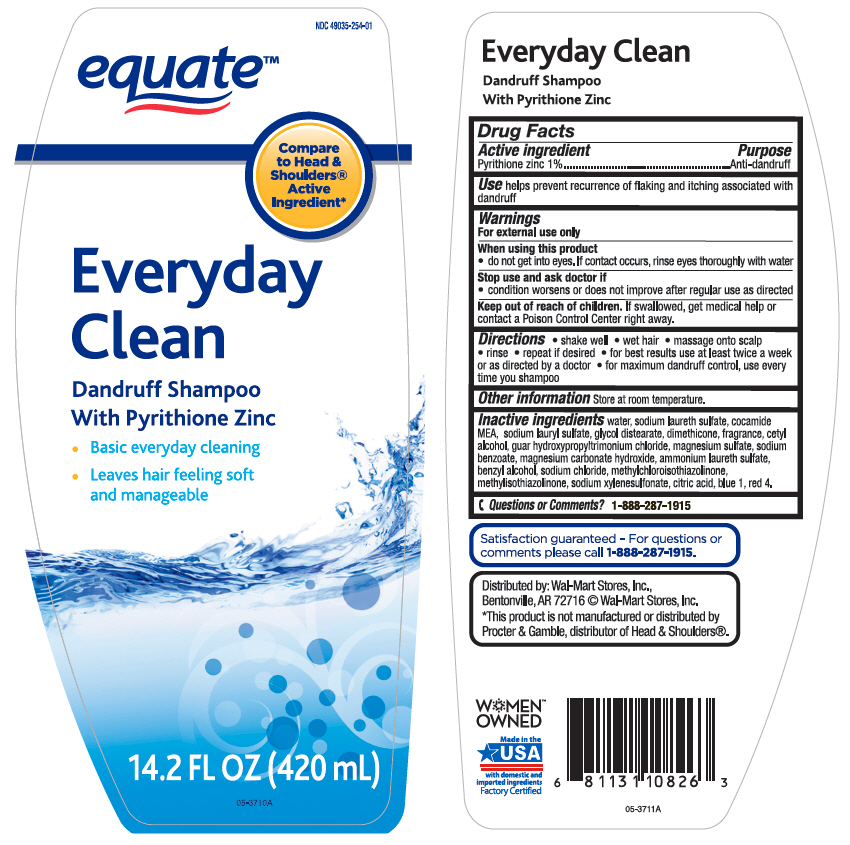 DRUG LABEL: Equate Everyday Clean Dandruff
NDC: 49035-254 | Form: SHAMPOO
Manufacturer: Wal-Mart Stores, Inc.
Category: otc | Type: HUMAN OTC DRUG LABEL
Date: 20240129

ACTIVE INGREDIENTS: Pyrithione Zinc 10 mg/1 mL
INACTIVE INGREDIENTS: Water; SODIUM LAURETH-3 SULFATE; COCO MONOETHANOLAMIDE; Sodium Lauryl Sulfate; Glycol Distearate; Dimethicone; Cetyl Alcohol; GUAR HYDROXYPROPYLTRIMONIUM CHLORIDE (1.7 SUBSTITUENTS PER SACCHARIDE); MAGNESIUM SULFATE, UNSPECIFIED FORM; Sodium Benzoate; Magnesium Carbonate Hydroxide; AMMONIUM LAURETH-5 SULFATE; Benzyl Alcohol; Sodium Chloride; Methylchloroisothiazolinone; Methylisothiazolinone; Sodium Xylenesulfonate; CITRIC ACID MONOHYDRATE; FD&C BLUE NO. 1; FD&C RED NO. 4

Equate™ Everyday Clean Dandruff Shampoo
Anti-Dandruff

Drug Facts

Active ingredient

Pyrithione Zinc 1%

Purpose

Anti-dandruff

Use

helps prevent recurrence of flaking and itching associated with dandruff

Warnings

For external use only

When using this product

- do not get into eyes. If contact occurs, rinse eyes thoroughly with water

Stop use and ask a doctor if

- condition worsens or does not improve after regular use as directed

Keep out of reach of children. If swallowed, get medical help or contact a Poison Control Center right away.

Directions

- shake well
- wet hair
- massage onto scalp
- rinse
- repeat if desired
- for best results use at least twice a week or as directed by a doctor
- for maximum dandruff control, use every time you shampoo

Other information

store at room temperature

Inactive ingredients

water, sodium laureth sulfate, cocamide MEA, sodium lauryl sulfate, glycol distearate, dimethicone, fragrance, cetyl alcohol, guar hydroxypropyltrimonium chloride, magnesium sulfate, sodium benzoate, magnesium carbonate hydroxide, ammonium laureth sulfate, benzyl alcohol, sodium chloride, methylchloroisothiazolinone, methylisothiazolinone, sodium xylenesulfonate, citric acid, blue 1, red 4

Questions or Comments?

1-888-287-1915

Distributed by: Wal-Mart Stores, Inc.,
Bentonville, AR 72716

PRINCIPAL DISPLAY PANEL - 420 mL Bottle Label

NDC 49035-254-01

equate™

Compare
to Head &
Shoulders®
Active
Ingredient*

Everyday
Clean

Dandruff Shampoo
With Pyrithione Zinc

- Basic everyday cleaning
- Leaves hair feeling soft
  and manageable

14.2 FL OZ (420 mL)

05-3710A